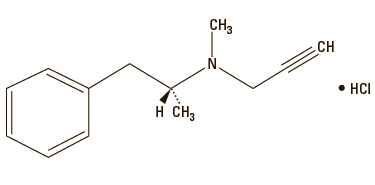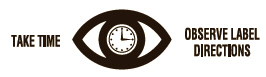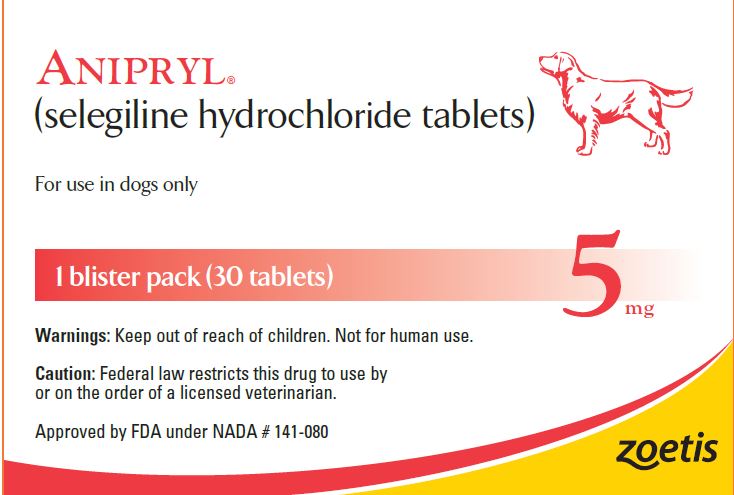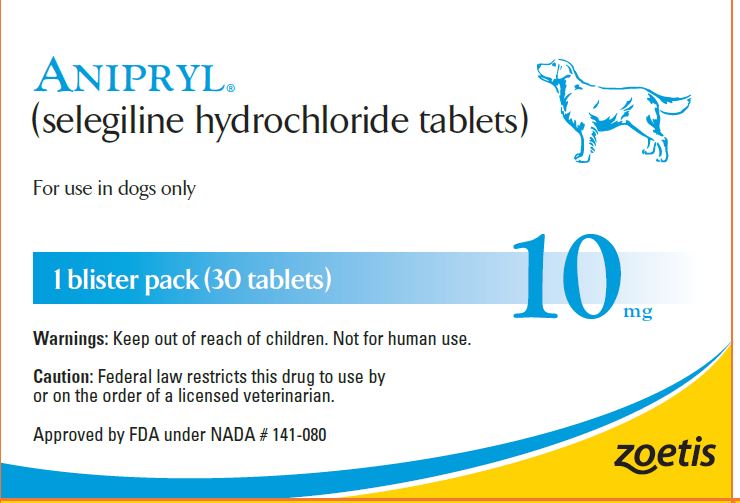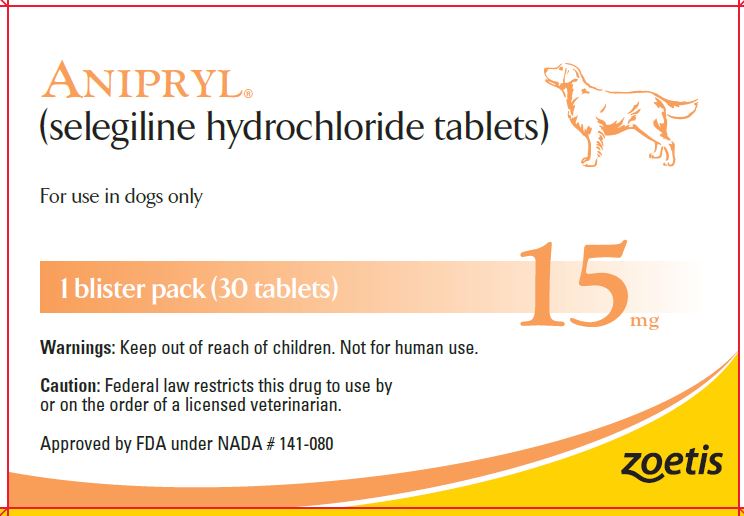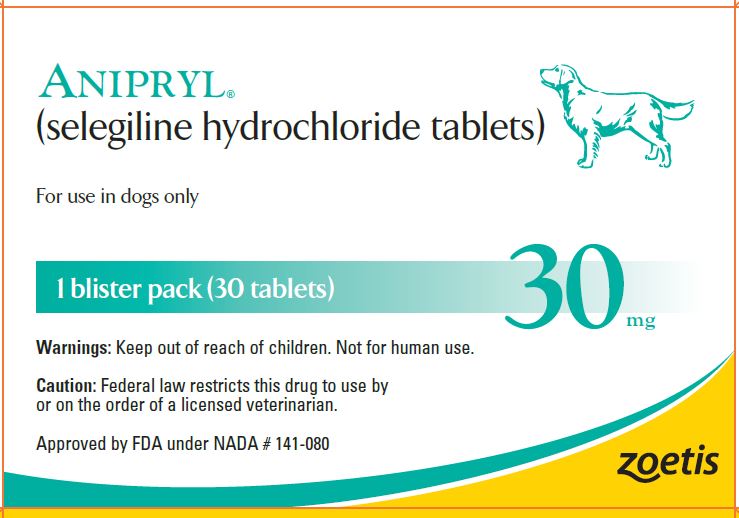 DRUG LABEL: ANIPRYL
NDC: 54771-8192 | Form: TABLET
Manufacturer: Zoetis Inc.
Category: animal | Type: PRESCRIPTION ANIMAL DRUG LABEL
Date: 20221213

ACTIVE INGREDIENTS: SELEGILINE HYDROCHLORIDE 5 mg/1 1

ANIPRYL®

ANIPRYL®

(selegiline hydrochloride tablets)

For use in dogs only

CAUTION

Federal law restricts this drug to use by or on the order of a licensed veterinarian.

DESCRIPTION

Anipryl (selegiline hydrochloride tablets) are white, convex tablets containing 5, 10, 15, and 30 mg of selegiline HCl. It is commonly referred to in the clinical and pharmacological literature as L-deprenyl (the levorotatory form of deprenyl HCl).

Selegiline hydrochloride is (—)-(R)-N,α-Dimethyl-N-2-propynylphenethylamine hydrochloride.

Molecular Formula: C13H17N HCl
Molecular Weight: 223.75

PHARMACOLOGY

Selegiline is an irreversible inhibitor of monoamine oxidase (MAO).^1,2 MAOs are widely distributed throughout the body and are subclassified into 2 types, A and B, which differ in their substrate specificity and tissue distribution. Selegiline is believed to be a selective inhibitor of MAO-B at recommended dosages in the dog due to its greater affinity for type B enzyme active sites compared to type A sites.^1 In CNS neurons, MAO plays a role in the catabolism of catecholamines, (dopamine, and, to a lesser extent, norepinephrine and epinephrine) and serotonin.^1,2 Selegiline may have pharmacologic effects unrelated to MAO-B inhibition. There is some evidence that it may increase dopaminergic activity by other mechanisms, including increasing synthesis and release of dopamine into the synapse as well as interfering with dopamine re-uptake from the synapse.^2–4 Effects resulting from selegiline administration may also be mediated through its metabolites. Two of its 3 principal metabolites, L-amphetamine and L-methamphetamine, have pharmacologic actions of their own. However, the extent to which these metabolites contribute to the effects of selegiline is unknown.

Therapeutic effects of selegiline are thought to result in part from enhanced catecholaminergic nerve function and increased dopamine levels in the CNS.^5,6 The pathogenesis of the development of clinical signs associated with cognitive decline is considered to be partly a result of a decrease in the level of catecholamines in the CNS and deficiencies in neurotransmission.^7 There is evidence which points to hypothalamic dopamine deficiency playing a role in the pathogenesis of pituitary dependent hyperadrenocorticism in the dog.^8,9

Based upon IV administration of selegiline to 4 mixed breed female dogs, the plasma elimination half-life was estimated to be 60 ± 10 minutes (mean ± SD) and the volume of distribution at steady-state (Vss) was estimated to be 9.4 ± 1.6 L/kg (mean ± SD). The relatively large Vss suggests that the selegiline is extensively distributed to body tissues. The absolute bioavailability, F, of an oral solution was less than 10%.^10

INDICATIONS

Anipryl tablets are indicated for the control of clinical signs associated with canine cognitive dysfunction syndrome (CDS) and control of clinical signs associated with uncomplicated canine pituitary dependent hyperadrenocorticism (PDH).

CONTRAINDICATIONS

Anipryl is contraindicated in patients with known hypersensitivity to this drug.
In humans, selegiline is contraindicated for use with meperidine and this contraindication is often extended to other opioids.

WARNINGS

Keep out of reach of children. Not for human use.
Anipryl should not be administered at doses exceeding those recommended (0.5–2.0 mg/kg once daily).
In humans, concurrent use of MAO inhibitors with alpha-2 agonists has resulted in extreme fluctuations of blood pressure; therefore, blood pressure monitoring is recommended with concurrent use in dogs. Also, in humans, severe CNS toxicity including death has been reported with the combination of selegiline and tricyclic antidepressants, and selegiline and selective serotonin reuptake inhibitors. Although no such adverse drug interactions were reported in the clinical trials in dogs, it seems prudent to avoid the combination of Anipryl and selective serotonin reuptake inhibitors (e.g., fluoxetine) as well as Anipryl and tricyclic (e.g., clomipramine, amitriptyline, imipramine) or other antidepressants.
At least 14 days should elapse between discontinuation of Anipryl and initiation of treatment with a tricyclic antidepressant or selective serotonin reuptake inhibitor. Because of the long half-life of fluoxetine and its active
metabolites, at least 5 weeks should elapse between discontinuation of fluoxetine and initiation of treatment with Anipryl.
Concurrent use of Anipryl with ephedrine or potential MAO inhibitors, such as amitraz, is not recommended.

PRECAUTIONS:

General

Anipryl is not recommended for other behavior problems such as aggression. In the clinical trials, 3 dogs showed an increase in aggression while on this drug. The safety and efficacy of Anipryl has not been evaluated in dogs with debilitating systemic diseases other than PDH.
The decision to prescribe Anipryl should take into consideration that the MAO system of enzymes is complex and incompletely understood and there is only a limited amount of carefully documented clinical experience with selegiline. Consequently, the full spectrum of possible responses to selegiline may not have been observed in pre-marketing evaluation of the drug. It is advisable, therefore, to observe patients carefully for atypical responses.
Endocrine function testing to confirm pituitary dependent hyperadrenocorticism should be performed prior to Anipryl administration for that condition. Anipryl is not recommended for treatment of patients with hyperadrenocorticism not of pituitary origin such as those due to an adrenal tumor or administration of glucocorticoids. If complications of PDH are evident at the time of diagnosis or emerge during Anipryl therapy, the patient should be evaluated and, if warranted, alternative therapy considered. Concurrent use of Anipryl in conjunction with other therapies of canine PDH has not been evaluated.

Laboratory Tests

No specific laboratory tests are deemed essential for the management of patients on Anipryl, as response to therapy should be based on the history and physical examinations for both PDH and CDS. In clinical trials for PDH, no correlation was found between an individual patient’s clinical response and results of the low dose dexamethasone suppression (LDDS) test. There was no evidence of adrenal insufficiency in these trials.
In the 12 week clinical trial for CDS, a small number of dogs had a drop in hematocrit; some dropping within the normal range and some dropping below 37%. The clinical significance of this is unknown at this time. It is advisable to conduct a thorough physical examination and to consider appropriate laboratory tests to establish hematological and serum biochemical baseline data prior to administration of Anipryl.

Reproductive Safety

The safety of Anipryl in breeding, pregnant and lactating bitches, and breeding dogs has not been determined.

ADVERSE REACTIONS

In clinical trials, 404 dogs treated with Anipryl for as long as 18 months were monitored for the occurrence of adverse events. Many of the observations listed in the following table may be associated with the underlying disease (PDH or CDS), the advanced age of the patients or the development of unrelated concurrent disease. One index of relative importance, however, is whether or not a reaction caused treatment discontinuation. Eighteen dogs (4%) experienced one or more of the following adverse events that led either to discontinuation of therapy with Anipryl, dismissal from the study, or a reduction in dose: restlessness/agitation, vomiting, disorientation, diarrhea, diminished hearing, possible drug interaction (weakness, confusion, incoordination and "seizure-like" activity while being treated concurrently with metronidazole, prednisone, and trimethoprim sulfa), increase in destructive behavior in a dog with separation anxiety, anorexia, anemia, stiffness and polydipsia.

Percentage of Dogs with Adverse Events Reported in Clinical Field Trials
Adverse Event | Anipryl (n=404) | Placebo (n=67)
vomiting | 26% | 21%
diarrhea | 18% | 10%
hyperactive/restless* | 12% | 6%
anorexia | 8% | 1%
neurologic** | 6% | 1%
lethargy | 6% | 1%
salivation | 5% | 4%
urinary tract infection | 4% | 1%
pruritus/dermatologic | 4% | 1%
weakness | 4% | 0
pale gums | 3% | 1%
polyuria/polydipsia | 3% | 1%
weight loss | 3% | 0
diminished hearing | 2% | 0
panting | 2% | 1%
cardiovascular/respiratory*** | 2% | 0
licking | 2% | 1%

*This includes hyperactivity, irritability, abnormal repetitive movements, anxiousness, and restlessness.
**This includes ataxia, incoordination, staggering, disorientation, decreased proprioception, and seizure.
***This includes heart murmurs, tachycardia, collapse, dyspnea, pleural effusion, and sneezing.

DOSAGE AND ADMINISTRATION:

CDS

The recommended dosage for oral administration for the control of clinical signs associated with CDS is 0.5–1.0 mg/kg once daily, preferably administered in the morning. Initially, dogs should be dosed to the nearest whole tablet. Adjustments should then be made based on response and tolerance to the drug.

PDH

The recommended dosage for the control of clinical signs associated with canine PDH is 1.0 mg/kg once daily, preferably administered in the morning. If no improvement is observed after 2 months of therapy, dosage may be increased to a maximum of 2.0 mg/kg once daily. If no improvement is seen after 1 month at the higher dose or if at any time clinical signs progress, the dog should be re-evaluated. In dogs whose clinical signs of PDH progress despite Anipryl therapy in the absence of concurrent disease, alternate therapy should be considered.
Dogs should be monitored closely for possible adverse events associated with any increase in dose.

Clinical Use of Anipryl in CDS

CDS is an age-related deterioration of cognitive abilities characterized by behavioral changes not wholly attributable to a general medical condition such as neoplasia, infection, or organ failure. CDS is typified by multiple cognitive impairments which affect the dog's function. In clinical trials, the observed behavioral changes associated with CDS in older dogs included: disorientation, decreased activity level, abnormal sleep/wake cycles, loss of housetraining, decreased or altered responsiveness to family members, and decreased or altered greeting behavior. In clinical trials, Anipryl was shown to be effective in controlling clinical signs associated with CDS. After 4 weeks of treatment, dogs treated with Anipryl showed significant improvement when compared to placebo-treated controls in sleeping patterns, house-training, and activity level. Some dogs showed increased improvement up to 3 months, however, onset, duration and magnitude of response varied with individual dogs.

The diagnosis of CDS in dogs is a diagnosis of exclusion, based on thorough behavioral and medical histories, in conjunction with appropriate diagnostic work-up and testing.^11 Periodic patient monitoring to evaluate the response and tolerance to the drug and for the presence of concurrent or new disease is recommended.

Clinical Use of Anipryl in PDH

Clinical signs of PDH seen in clinical trials included panting, reduced activity, polydipsia, polyuria, changes in sleep patterns, altered appetite, obesity, alopecia, abdominal distention, reduced skin elasticity, thin skin, poor hair growth, pyoderma, decreased responsiveness to attention, and decreased enthusiasm of greeting. In clinical studies involving 125 evaluable cases of naturally occurring PDH, Anipryl was shown to be effective in controlling clinical signs associated with the disease. On physical examination, abdominal distention was the parameter which most consistently improved following treatment with Anipryl. Based on owner assessments, activity level was the parameter most consistently evaluated as "improved." Approximately 60% of the dogs were evaluated by the veterinarians and owners to be "slightly improved" to "improved" after 1 month of Anipryl therapy. By month 2, veterinarians reported that approximately 77% were "slightly improved" to "improved." Approximately 20% of dogs did not respond to Anipryl and were deemed treatment failures.

Those dogs that responded to Anipryl tended to do so within 1–2 months after treatment was initiated. Response to therapy varied between patients with some dogs showing improvement in all presenting clinical signs and others showing improvement in only 1–2 parameters. Duration of response was also variable, with some dogs continuing on Anipryl for over 1 year with good control of clinical signs and others showing an initial response to therapy only to be followed within several months by recurrence of clinical signs of PDH. There was no correlation demonstrated between an individual dog's clinical response to Anipryl and that dog's low dose dexamethasone suppression test results, therefore, monitoring should be based on history and physical examination findings.

SAFETY

In a laboratory safety study, Anipryl was administered orally to healthy adult beagles once daily for 6 months at doses of 0, 1, 2, 3, or 6 mg/kg (0.5x, 1x, 1.5x and 3x the maximum recommended daily dose of 2.0 mg/kg). The drug was demonstrated to be safe at the recommended dose range of 0.5–2.0 mg/kg. The following statistically significant clinical observations were noted in dogs in the 1.5x and 3x group: salivation, decreased pupillary response, and decreased body weight despite normal to increased feed consumption. Additional reactions seen at the 3x dose included panting, decreased skin elasticity (dehydration) and stereotypic behaviors, i.e., weaving (repetitive left to right movement) in the cage. This repetitive movement started several hours after dosing but was no longer present at the time of the next morning dose. There were no changes noted in blood pressure, heart rate and ECG parameters, nor were there any ophthalmic changes.

REFERENCES

1. Milgram NW, Ivy GO, Murphy MP, et al: Effects of chronic oral administration of L-deprenyl in the dog. Pharmacol Biochem Behav 51:421–428, 1995.

2. Heinonen EH, Lammintausta R: A review of the pharmacology of selegiline. Acta Neurol Scand 84:(suppl. 136): 44–59, 1991.

3. Knoll J: R-(-)Deprenyl (selegiline, Movergan®) facilitates the activity of the nigrostriatal dopaminergic neuron. J Neural Transm (suppl. 25):45–66, 1987.

4. Heikkila RE, Cabbat FS, Manzino L, et al: Potentiation by deprenil of l-dopa induced circling in nigral-lesioned rats. Pharmacol Biochem Behav 15:75–79, 1981.

5. Knoll J, Miklya I, Knoll B, et al: (-)Deprenyl and (-)1-phenyl-2-propylaminopentane, [(-) PPAP], act primarily as potent stimulants of action potential - transmitter release coupling in the catecholaminergic neurons. Life Sci 58:817–827, 1996.

6. Riederer P, Youdim MBH, Rausch WD, et al: On the mode of action of L-deprenyl in the human central nervous system. J Neural Transm 43:217–226, 1978.

7. Arnsten, AFT: Catecholamine mechanisms in age-related cognitive decline. Neurobiol Aging 14:639–641, 1993.

8. Peterson ME, Palkovits M, Chiueh CC, et al: Biogenic amine and corticotropin-releasing factor concentrations in hypothalamic paraventricular nucleus and biogenic amine levels in the median eminence of normal dogs, chronic dexamethasone-treated dogs, and dogs with naturally-occurring pituitary-dependent hyperadrenocorticism (Canine Cushing's Disease). J Neuroendocrinology 1:169–171, 1989.

9. Bruyette DS, Ruehl WW, Entriken TL, et al: Treating canine pituitary-dependent hyperadrenocorticism with L-deprenyl. Veterinary Medicine 92:711–727, 1997.

10. Mahmood I, Peters DK, Mason WD: The pharmacokinetics and absolute bioavailability of selegiline in the dog. Biopharm Drug Dispos 15:653–664, 1994.

11. Ruehl WW, Hart BL: Canine cognitive dysfunction, in Dodman N, Shuster L (eds): Psychopharmacology of Animal Behavior Disorders. Cambridge, MA, Blackwell Science, Inc. 1998.

HOW SUPPLIED

Four tablet strengths are available in blister-packs of 30 tablets each: 5 mg, 10 mg, 15 mg, and 30 mg. Each box contains 1 blister pack (30 tablets).

STORAGE

Store at controlled room temperature 20°–25°C (68°–77°F).

For a copy of the Safety Data Sheet (SDS) or to report adverse reactions call Zoetis Inc. at 1-888-963-8471.

Approved by FDA under NADA # 141-080
zoetis
Distributed by:
Zoetis Inc.
Kalamazoo, MI 49007
51027800
Revised: July 2019